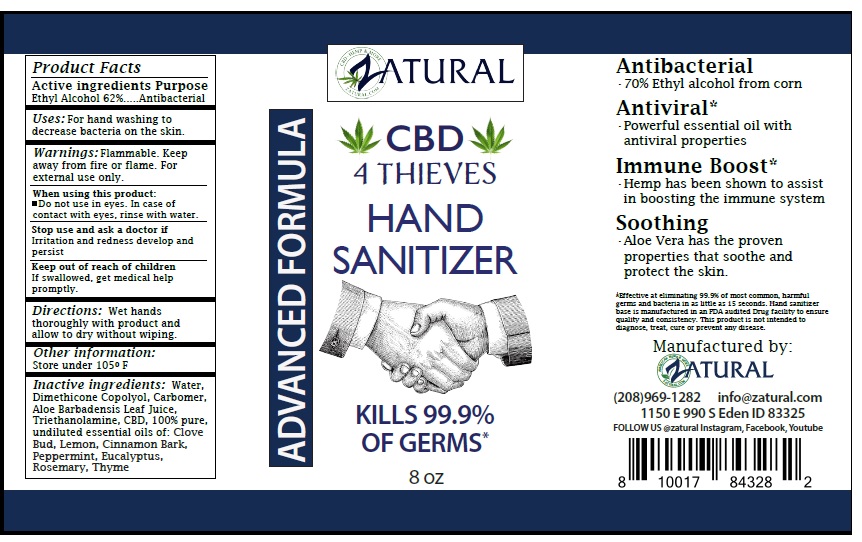 DRUG LABEL: ZATURAL HAND SANITIZER
NDC: 77615-100 | Form: LIQUID
Manufacturer: Prospinach, LLC
Category: otc | Type: HUMAN OTC DRUG LABEL
Date: 20220117

ACTIVE INGREDIENTS: ALCOHOL 62 L/100 L
INACTIVE INGREDIENTS: WATER; PEG/PPG-18/18 DIMETHICONE; CARBOMER HOMOPOLYMER, UNSPECIFIED TYPE; ALOE VERA LEAF; TROLAMINE; CANNABIS SATIVA SEED OIL; CLOVE OIL; LEMON OIL, COLD PRESSED; CINNAMON BARK OIL; PEPPERMINT OIL; EUCALYPTUS OIL; ROSEMARY OIL; THYME OIL

ZATURAL CBD 4 THIEVES HAND SANITIZER

Active ingredients

Ethyl Alcohol 62%

Purpose

Antibacterial

INDICATIONS AND USAGE

Uses: For hand washing to decrease bacteria on the skin.

WARNINGS

Warnings: Flammable. Keep way from fire or flame. For external use only.

When using this product: • Do not use in eyes. In case of contact with eyes, rinse with water.
Stop use and ask a doctor if Irritation and redness develop and persist

Keep out of reach of children If swallowed, get medical help promptly.

DOSAGE AND ADMINISTRATION

Directions: Wet hands thoroughly with product and allow to dry without wiping.

Other information:

Store under 105º F

INACTIVE INGREDIENT

Inactive ingredients: Water, Dimethicone Copolyol, Carbomer, Aloe Barbadensis Leaf Juice, Triethanolamine, CBD, 100% pure, undiluted essential oils of: Clove Bud, Lemon, Cinnamon Bark, Peppermint, Eucalyptus, Rosemary, Thyme

ADVANCED FORMULA

KILLS 99.9% OF GERMS*

Antibacterial
•70% Ethyl alcohol from corn

Antiviral*
•Powerful essential oil with antiviral properties

Immune Boost*
•Hemp has been shown to assist in boosting the immune system

Soothing
•Aloe Vera has the proven properties that soothe and protect the skin.

*Effective at eliminating 99.9% of most common, harmful germs and bacteria in as little as 15 seconds. Hand sanitizer base is manufactured in an FDA audited Drug facility to ensure quality and consistency. This product is not intended to diagnose, treat, cure or prevent any disease.

Manufactured by: ZATURAL

(208)969-1282 info@zatural.com
1150 E 990 S Eden ID 83325
FOLLOW US @zatural Instagram, Facebook, Youtube